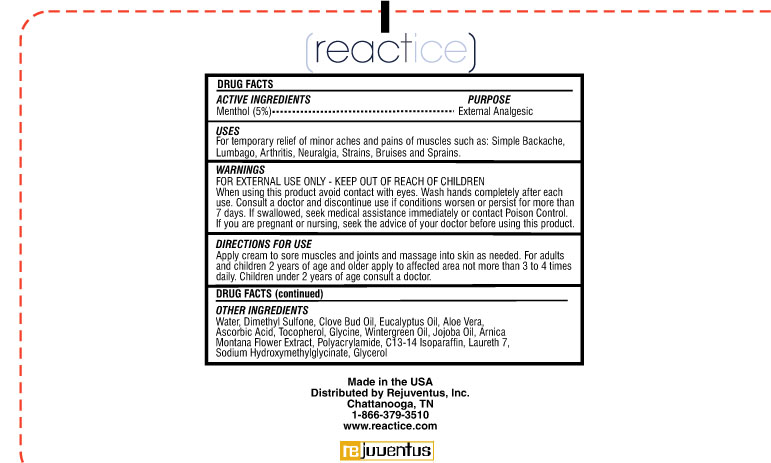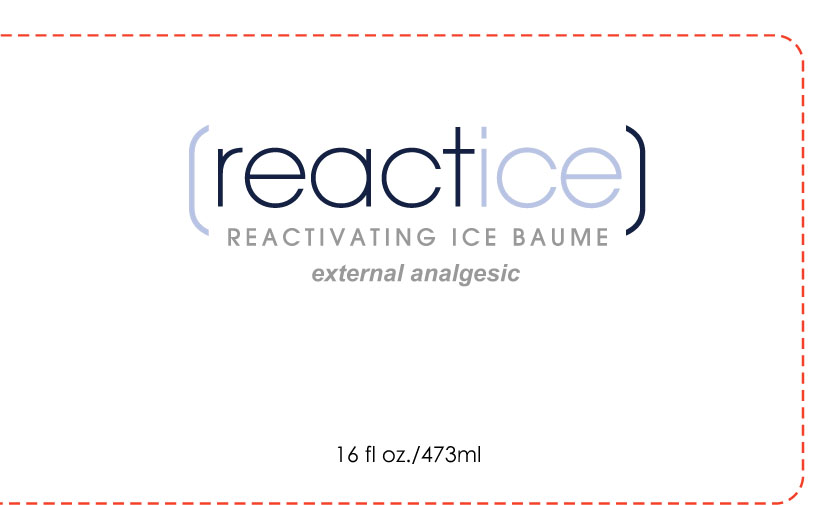 DRUG LABEL: Reactice
NDC: 75963-125 | Form: CREAM
Manufacturer: Rejuventus, Inc.
Category: otc | Type: HUMAN OTC DRUG LABEL
Date: 20120127

ACTIVE INGREDIENTS: MENTHOL 118.29 mL/100 mL
INACTIVE INGREDIENTS: DIMETHYL SULFONE; CLOVE; PEPPERMINT OIL; EUCALYPTUS OIL; ALOE VERA LEAF; ASCORBIC ACID; TOCOPHEROL; GLYCINE; JOJOBA OIL; ARNICA MONTANA FLOWER; C13-14 ISOPARAFFIN; LAURETH-7; SODIUM HYDROXYMETHYLGLYCINATE; GLYCERIN

Reactice Reactivating Ice Baume

Active ingredients Purpose

Menthol (5%) External Analgesic

Uses

For temporary relief of minor aches and pains of muscles such as: simple backache, lumbago, arthritis, neuralgia, strains, bruises, strains, bruises, and sprains

Keep out of reach of children

INDICATIONS AND USAGE

Consult a doctor and discontinue use if conditions worsen or persist for more than 7 days.

WARNINGS

For External use only. When using this product avoid contact with eyes. Wash hands completely after each use. If swallowed seek medical assistance immediately or contact poison control. If you are pregnant or nursing,seek the advice of your doctor before using this product.

DOSAGE AND ADMINISTRATION

Directions for use

Apply cream to sore muscles and joints and massage into skin as needed. For adults and children 2 years of age and older apply to affected area not more than 3 to 4 times daily. Children under 2 years of age consult a doctor.

INACTIVE INGREDIENT

Water, Dimethyl Sulfone, Clove bud oil, Peppermint oil, Eucalyptus oil, Aloe Vera, Ascorbic acid, Tocopherol, Glycine, Wintergreen oil, Jojoba oil, Arnica Montana Flower Extract, Polyacrylamide, C13-14 Isoparaffin, Laureth 7, Sodium Hydroxymethylglycinate, glycerol.

PACKAGE LABEL

Reactice

Reactivating Ice Baume

external analgesic

16 fl oz./473ml